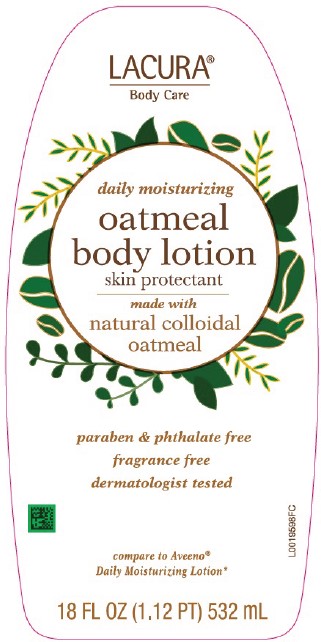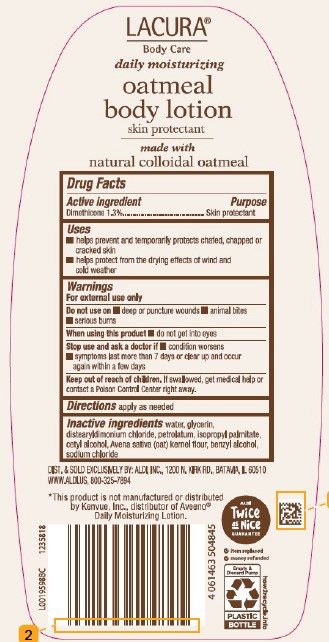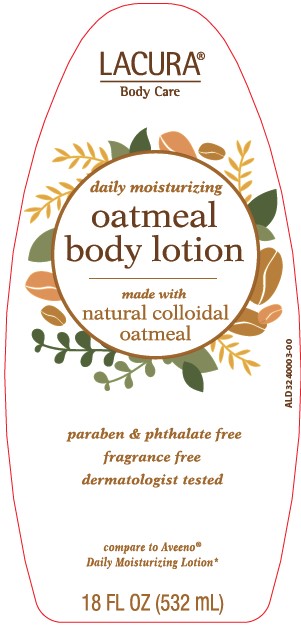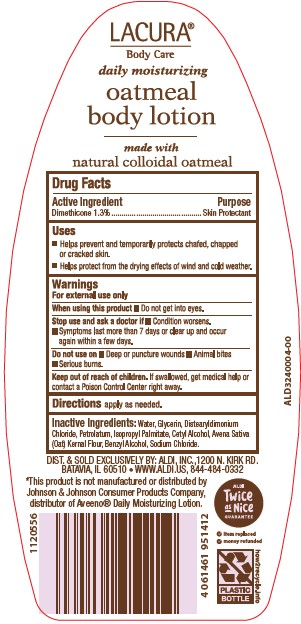 DRUG LABEL: Daily Moisturizing
NDC: 64024-619 | Form: LOTION
Manufacturer: Aldi, Inc
Category: otc | Type: HUMAN OTC DRUG LABEL
Date: 20260129

ACTIVE INGREDIENTS: DIMETHICONE 13.13 mg/1 mL
INACTIVE INGREDIENTS: WATER; GLYCERIN; DISTEARYLDIMONIUM CHLORIDE; PETROLATUM; ISOPROPYL PALMITATE; CETYL ALCOHOL; OATMEAL; BENZYL ALCOHOL; SODIUM CHLORIDE

Lacura 619.003/619AC rev 2
Daily Moisturizing Lotion

Claims

LACURA

Body Care

daily moisturizing

oatmeal

body lotion

skin protectant

made with natural colloidal oatmeal

Active ingredient

Dimethicone 1.3%

Purpose

Skin Protectant

Uses

- helps prevent and temporarily protects chafed, chapped or cracked skin
- helps protect from the drying effects of wind and cold weather

Warnings

For external use only

Do not use on

- deep or punture wounds
- animal bites
- serious burns

When using this product

- do not get into eyes

Stop use and ask a doctor if

- condition worsens
- symptoms last more than 7 days or clear up and occur again within a few days

Keep out of reach of children.

If swallowed, get medical help or contact a Poison Control Center right away.

Directions

apply as needed.

Inactive ingredients

water, glycerin, distearyldimonium chloride, petrolatum, isopropyl palmitate, cetyl alcohol, Avena sativa (oat) kernel flour, benzyl alcohol, sodium chloride

ADVERSE REACTION

DIST. & SOLD EXCLUSIVELY BY: ALDI INC., 1200 N. KIRK RD., BATAVIA, IL 60510

WWW.ALDLUS, 800-325-7894

ALDI TWICE AS NICE GUARANTEE

- item replaced
- money refunded

Empty & Discard Pump

PLASTIC BOTTLE

how2recycle.info

Disclaimer

*This product is not manufactured or distributed by Kenvue, Inc., distributor of Aveno® Daily Moisturizing Lotion.

principal display panel

LACURA®

Body Care

daily moisturizing

oatmeal

body lotion

made with natural colloidal oatmeal

paraben & phthalate free

fragrance free

dermatologist tested

compare to Aveeno®Daily Mositurizing Lotion*

18 FL OZ (1.12 PT) 532 mL

PRINCIPAL DISPLAY PANEL

LACURA®

Body Care

daily moisturizing

oatmeal body lotion

made with natural colloidal oatmeal

paraben & phthalate free

fragrance free

dermatologist test

compare to Aveeno® Daily Moisturizing Lotion*

18 FL OZ (532 mL)